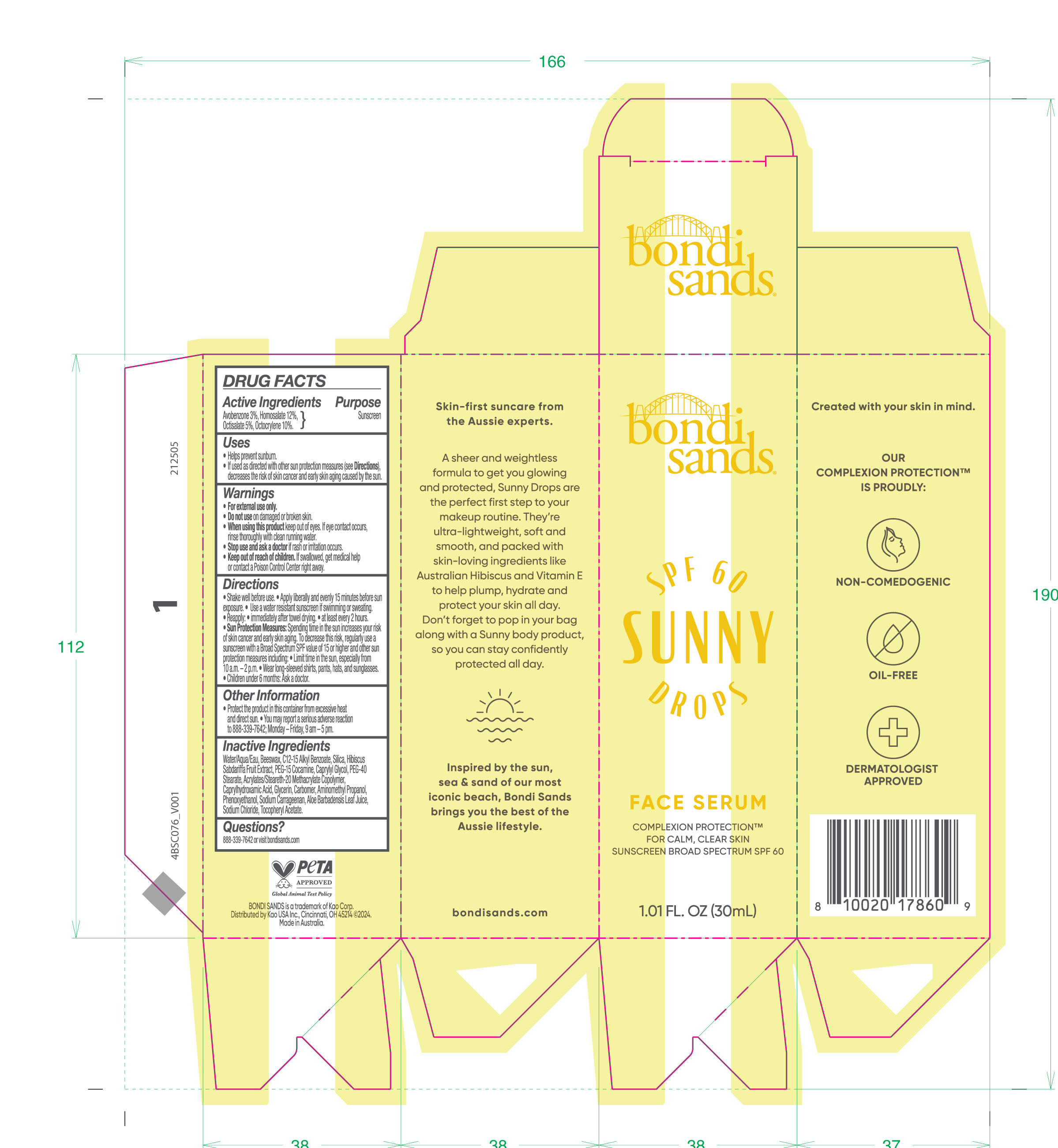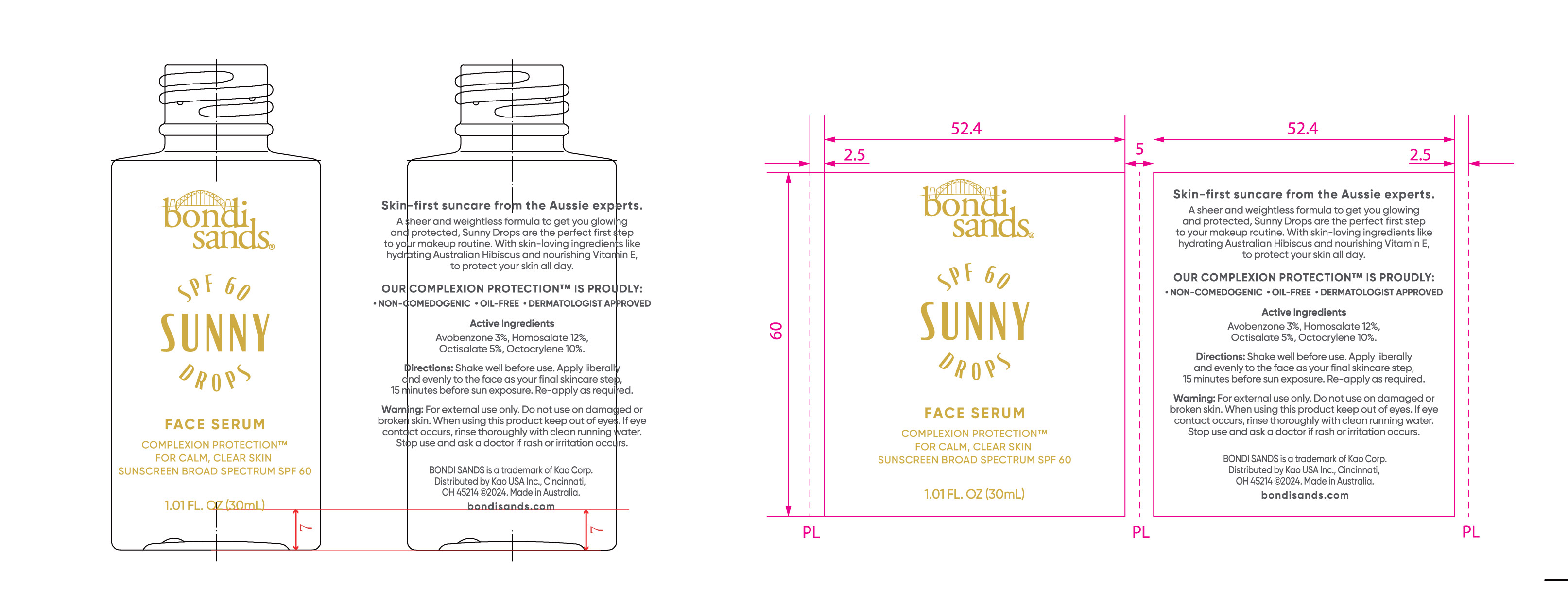 DRUG LABEL: Bondi Sands Broad Spectrum SPF 60 Sunny Drops Face Serum
NDC: 70157-023 | Form: SOLUTION/ DROPS
Manufacturer: Baxter Laboratories Pty. Ltd. 
Category: otc | Type: HUMAN OTC DRUG LABEL
Date: 20251027

ACTIVE INGREDIENTS: HOMOSALATE 12 g/100 mL; OCTOCRYLENE 10 g/100 mL; AVOBENZONE 3 g/100 mL; OCTISALATE 5 g/100 mL
INACTIVE INGREDIENTS: C12-15 ALKYL BENZOATE; GLYCERIN; .ALPHA.-TOCOPHEROL ACETATE; SILICON DIOXIDE; PEG-15 COCAMINE; PHENOXYETHANOL; BEESWAX; SODIUM CARRAGEENAN; CAPRYLYL GLYCOL; WATER; AMINOMETHYL PROPANOL; SODIUM CHLORIDE; ACRYLATES/STEARETH-20 METHACRYLATE COPOLYMER; ALOE BARBADENSIS LEAF; CAPRYLHYDROXAMIC ACID; HIBISCUS SABDARIFFA WHOLE; PEG-40 STEARATE; CARBOMER

Bondi Sands Broad Spectrum SPF 60 Sunny Drops Face Serum

Active Ingredients Purpose

Avobenzone 3%, Homosalate 12%, Octisalate 5%, Octocrylene 10% Sunscreen

Uses

- Helps prevent sunburn.
- If used as directed with other sun protection measures (see Directions), decreases the risk of skin cancer and early skin aging caused by the sun.

- Keep out of reach of children. If swallowed, get medical help or contact a Poison Control Center right away.

- Stop use and ask a doctor if rash or irritation occurs.

Warnings

- For external use only.
- Do not use on damaged or broken skin.
- When using this product keep out of eyes. If eye contact occurs, rinse thoroughly with clean running water.

Directions

- Shake well before use.
- Apply liberally and evenly 15 minutes before sun exposure.
- Use a water resistant sunscreen if swimming or sweating.
- Reapply: immediately after towel drying.
  - at least every 2 hours.
- Sun Protection Measures: Spending time in the sun increases your risk of skin cancer and early skin aging. To decrease this risk, regularly use a sunscreen with a Broad Spectrum SPF value of 15 or higher and other sun protection measures including:
- Limit time in the sun, especially from 10 a.m.-2 p.m.
- Wear long-sleeved shirts, pants, hats, and sunglasses.
- Children under 6 months: Ask a doctor.

Inactive Ingredients

Water/Aqua/Eau, Beeswax, C12-15 Alkyl Benzoate, Silica, Hibiscus Sabdariffa Fruit Extract, PEG-15 Cocamine, Caprylyl Glycol, PEG-40 Stearate, Acrylates/Steareth-20 Methacrylate Copolymer, Caprylhydroxamic Acid, Glycerin, Carbomer, Aminomethyl Propanol, Phenoxyethanol, Sodium Carrageenan, Aloe Barbadensis Leaf Juice, Sodium Chloride, Tocopheryl Acetate.

Other Information

- Protect the product in this container from excessive heat and direct sun. You may report a serious adverse reaction to 888-339-7642; Monday-Friday, 9 am-5 pm.

PACKAGE LABEL

bondi sands

SPF 60 SUNNY DROPS

FACE SERUM

COMPLEXION PROTECTION

FOR CALM, CLEAR SKIN

SUNSCREEN BROAD SPECTRUM SPF 60

1.01 FL. OZ (30mL)